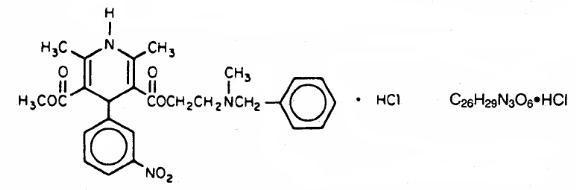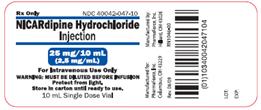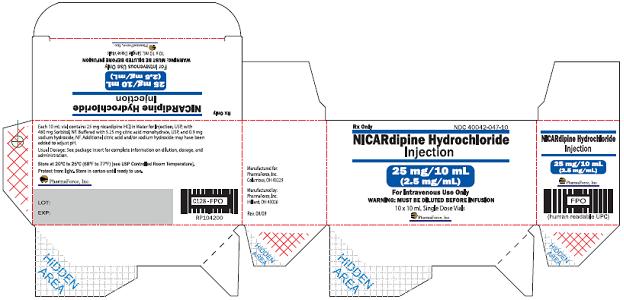 DRUG LABEL: Nicardipine Hydrochloride
NDC: 40042-047 | Form: INJECTION, SOLUTION
Manufacturer: PharmaForce, Inc.
Category: prescription | Type: HUMAN PRESCRIPTION DRUG LABEL
Date: 20091117

ACTIVE INGREDIENTS: NICARDIPINE HYDROCHLORIDE 2.5 mg/1 mL
INACTIVE INGREDIENTS: SORBITOL 48 mg/1 mL; CITRIC ACID MONOHYDRATE; SODIUM HYDROXIDE; WATER

Nicardipine Hydrochloride Injection

Rx Only

DESCRIPTION

Nicardipine hydrochloride is a calcium ion influx inhibitor (slow channel blocker or calcium channel blocker). Nicardipine hydrochloride injection for intravenous administration contains 2.5 mg/mL of nicardipine hydrochloride. Nicardipine hydrochloride is a dihydropyridine derivative with IUPAC (International Union of Pure and Applied Chemistry) chemical name (±)-2-(benzyl-methyl amino) ethyl methyl 1,4-dihydro-2, 6-dimethyl-4-(m-nitrophenyl)-3,5-pyridinedicarboxylate monohydrochloride and has the following structure:

Nicardipine hydrochloride is a greenish-yellow, odorless, crystalline powder that melts at about 169º C. It is freely soluble in chloroform, methanol, and glacial acetic acid, sparingly soluble in anhydrous ethanol, slightly soluble in n-butanol, water, 0.01 M potassium dihydrogen phosphate, acetone, and dioxane, very slightly soluble in ethyl acetate, and practically insoluble in benzene, ether, and hexane. It has a molecular weight of 515.99.

Nicardipine hydrochloride injection is available as a sterile, non-pyrogenic, clear, yellow solution in 10 mL vials for intravenous infusion after dilution. Each mL contains 2.5 mg nicardipine hydrochloride in water for injection, USP with 48 mg sorbitol, NF, buffered to pH 3.5 with 0.525 mg citric acid monohydrate, USP and 0.09 mg sodium hydroxide, NF. Additional citric acid and/or sodium hydroxide may have been added to adjust pH.

CLINICAL PHARMACOLOGY

Mechanism of Action

Nicardipine inhibits the transmembrane influx of calcium ions into cardiac muscle and smooth muscle without changing serum calcium concentrations. The contractile processes of cardiac muscle and vascular smooth muscle are dependent upon the movement of extracellular calcium ions into these cells through specific ion channels. The effects of nicardipine are more selective to vascular smooth muscle than cardiac muscle. In animal models, nicardipine produced relaxation of coronary vascular smooth muscle at drug levels which cause little or no negative inotropic effect.

Pharmacokinetics and Metabolism

Following infusion, nicardipine plasma concentrations decline tri-exponentially, with a rapid early distribution phase (α-half-life of 2.7 minutes), an intermediate phase (β-half-life of 44.8 minutes), and a slow terminal phase (γ-half-life of 14.4 hours) that can only be detected after long-term infusions. Total plasma clearance (Cl) is 0.4 L/hr•kg, and the apparent volume of distribution (Vd) using a non-compartment model is 8.3 L/kg. The pharmacokinetics of nicardipine hydrochloride injection are linear over the dosage range of 0.5 to 40 mg/hr.

Rapid dose-related increases in nicardipine plasma concentrations are seen during the first two hours after the start of an infusion of nicardipine hydrochloride injection. Plasma concentrations increase at a much slower rate after the first few hours, and approach steady state at 24 to 48 hours. On termination of the infusion, nicardipine concentrations decrease rapidly, with at least a 50% decrease during the first two hours post-infusion. The effects of nicardipine on blood pressure significantly correlate with plasma concentrations.

Nicardipine is highly protein bound (>95%) in human plasma over a wide concentration range.

Nicardipine hydrochloride injection has been shown to be rapidly and extensively metabolized by the liver. After coadministration of a radioactive intravenous dose of nicardipine hydrochloride injection with an oral 30 mg dose given every 8 hours, 49% of the radioactivity was recovered in the urine and 43% in the feces within 96 hours. None of the dose was recovered as unchanged nicardipine.

Nicardipine does not induce or inhibit its own metabolism and does not induce or inhibit hepatic microsomal enzymes.

The steady-state pharmacokinetics of nicardipine are similar in elderly hypertensive patients (>65 years) and young healthy adults.

Hemodynamics

Nicardipine hydrochloride injection produces significant decreases in systemic vascular resistance. In a study of intra-arterially administered nicardipine hydrochloride injection, the degree of vasodilation and the resultant decrease in blood pressure were more prominent in hypertensive patients than in normotensive volunteers. Administration of nicardipine hydrochloride injection to normotensive volunteers at dosages of 0.25 to 3 mg/hr for eight hours produced changes of <5 mmHg in systolic blood pressure and <3 mmHg in diastolic blood pressure.

An increase in heart rate is a normal response to vasodilation and decrease in blood pressure; in some patients these increases in heart rate may be pronounced. In placebo-controlled trials, the mean increases in heart rate were 7 ± 1 bpm in postoperative patients and 8 ± 1 bpm in patients with severe hypertension at the end of the maintenance period.

Hemodynamic studies following intravenous dosing in patients with coronary artery disease and normal or moderately abnormal left ventricular function have shown significant increases in ejection fraction and cardiac output with no significant change, or a small decrease, in left ventricular end-diastolic pressure (LVEDP). There is evidence that nicardipine hydrochloride increases blood flow. Coronary dilatation induced by nicardipine hydrochloride injection improves perfusion and aerobic metabolism in areas with chronic ischemia, resulting in reduced lactate production and augmented oxygen consumption. In patients with coronary artery disease, nicardipine hydrochloride injection, administered after beta-blockade, significantly improved systolic and diastolic left ventricular function.

In congestive heart failure patients with impaired left ventricular function, nicardipine hydrochloride injection increased cardiac output both at rest and during exercise. Decreases in left ventricular end-diastolic pressure were also observed. However, in some patients with severe left ventricular dysfunction, it may have a negative inotropic effect and could lead to worsened failure.

“Coronary steal” has not been observed during treatment with nicardipine hydrochloride injection. (Coronary steal is the detrimental redistribution of coronary blood flow in patients with coronary artery disease from underperfused areas toward better perfused areas.) Nicardipine hydrochloride injection has been shown to improve systolic shortening in both normal and hypokinetic segments of myocardial muscle. Radionuclide angiography has confirmed that wall motion remained improved during increased oxygen demand. (Occasional patients have developed increased angina upon receiving nicardipine hydrochloride capsules. Whether this represents coronary steal in these patients, or is the result of increased heart rate and decreased diastolic pressure, is not clear.)

In patients with coronary artery disease, nicardipine hydrochloride injection improves left ventricular diastolic distensibility during the early filling phase, probably due to a faster rate of myocardial relaxation in previously underperfused areas. There is little or no effect on normal myocardium, suggesting the improvement is mainly by indirect mechanisms such as afterload reduction and reduced ischemia. Nicardipine hydrochloride injection has no negative effect on myocardial relaxation at therapeutic doses. The clinical benefits of these properties have not yet been demonstrated.

Electrophysiologic Effects

In general, no detrimental effects on the cardiac conduction system have been seen with nicardipine hydrochloride injection. During acute electrophysiologic studies, it increased heart rate and prolonged the corrected QT interval to a minor degree. It did not affect sinus node recovery or SA conduction times. The PA, AH, and HV intervals1 or the functional and effective refractory periods of the atrium were not prolonged. The relative and effective refractory periods of the His-Purkinje system were slightly shortened.

^1PA = conduction time from high to low right atrium; AH = conduction time from low right atrium to His bundle deflection, or AV nodal conduction time; HV = conduction time through the His bundle and the bundle branch-Purkinje system.

Hepatic Function

Because nicardipine is extensively metabolized by the liver, plasma concentrations are influenced by changes in hepatic function. In a clinical study with nicardipine hydrochloride capsules in patients with severe liver disease, plasma concentrations were elevated and the half-life was prolonged (see PRECAUTIONS). Similar results were obtained in patients with hepatic disease when nicardipine hydrochloride injection was administered for 24 hours at 0.6 mg/hr.

Renal Function

When nicardipine hydrochloride injection was given to mild to moderate hypertensive patients with moderate degrees of renal impairment, significant reduction in glomerular filtration rate (GFR) and effective renal plasma flow (RPF) was observed. No significant differences in liver blood flow were observed in these patients. A significantly lower systemic clearance and higher area under the curve (AUC) were observed.

When nicardipine hydrochloride capsules (20 mg or 30 mg TID) were given to hypertensive patients with impaired renal function, mean plasma concentrations, AUC, and Cmax were approximately two-fold higher than in healthy controls. There is a transient increase in electrolyte excretion, including sodium (see PRECAUTIONS).

Acute bolus administration of nicardipine hydrochloride injection (2.5 mg) in healthy volunteers decreased mean arterial pressure and renal vascular resistance; glomerular filtration rate (GFR), renal plasma flow (RPF), and the filtration fraction were unchanged. In healthy patients undergoing abdominal surgery, nicardipine hydrochloride injection (10 mg over 20 minutes) increased GFR with no change in RPF when compared with placebo. In hypertensive type II diabetic patients with nephropathy, nicardipine hydrochloride capsules (20 mg TID) did not change RPF and GFR, but reduced renal vascular resistance.

Pulmonary Function

In two well-controlled studies of patients with obstructive airway disease treated with nicardipine hydrochloride capsules, no evidence of increased bronchospasm was seen. In one of the studies, nicardipine hydrochloride capsules improved forced expiratory volume 1 second (FEV1) and forced vital capacity (FVC) in comparison with metoprolol. Adverse experiences reported in a limited number of patients with asthma, reactive airway disease, or obstructive airway disease are similar to all patients treated with nicardipine hydrochloride capsules.

Effects in Hypertension

In patients with mild to moderate chronic stable essential hypertension, nicardipine hydrochloride injection (0.5 to 4 mg/hr) produced dose-dependent decreases in blood pressure, although only the decreases at 4 mg/hr were statistically different from placebo. At the end of a 48-hour infusion at 4 mg/hr, the decreases were 26 mmHg (17%) in systolic blood pressure and 20.7 mmHg (20%) in diastolic blood pressure. In other settings (e.g., patients with severe or postoperative hypertension), nicardipine hydrochloride injection (5 to 15 mg/hr) produced dose-dependent decreases in blood pressure. Higher infusion rates produced therapeutic responses more rapidly. The mean time to therapeutic response for severe hypertension, defined as diastolic blood pressure ≤ 95 mmHg or ≥ 25 mmHg decrease and systolic blood pressure ≤160 mmHg, was 77 ± 5.2 minutes. The average maintenance dose was 8 mg/hr. The mean time to therapeutic response for postoperative hypertension, defined as ≥15% reduction in diastolic or systolic blood pressure, was 11.5 ± 0.8 minutes. The average maintenance dose was 3 mg/hr.

INDICATIONS AND USAGE

Nicardipine hydrochloride injection is indicated for the short-term treatment of hypertension when oral therapy is not feasible or not desirable.

For prolonged control of blood pressure, patients should be transferred to oral medication as soon as their clinical condition permits (see DOSAGE AND ADMINISTRATION).

CONTRAINDICATIONS

Nicardipine hydrochloride injection is contraindicated in patients with known hypersensitivity to the drug. Nicardipine hydrochloride injection is also contraindicated in patients with advanced aortic stenosis because part of the effect of nicardipine hydrochloride injection is secondary to reduced afterload. Reduction of diastolic pressure in these patients may worsen rather than improve myocardial oxygen balance.

WARNINGS

Beta-Blocker Withdrawal

Nicardipine is not a beta-blocker and therefore gives no protection against the dangers of abrupt beta-blocker withdrawal; any such withdrawal should be by gradual reduction of dose of beta-blocker.

Rapid Decreases in Blood Pressure

No clinical events have been reported suggestive of a too rapid decrease in blood pressure with nicardipine hydrochloride injection. However, as with any antihypertensive agent, blood pressure lowering should be accomplished over as long a time as is compatible with the patient’s clinical status.

Use in Patients with Angina

Increases in frequency, duration, or severity of angina have been seen in chronic oral therapy with nicardipine hydrochloride capsules. Induction or exacerbation of angina has been seen in less than 1% of coronary artery disease patients treated with nicardipine hydrochloride injection. The mechanism of this effect has not been established.

Use in Patients with Congestive Heart Failure

Nicardipine hydrochloride injection reduced afterload without impairing myocardial contractility in preliminary hemodynamic studies of CHF patients. However, in vitro and in some patients, a negative inotropic effect has been observed. Therefore, caution should be exercised when using nicardipine hydrochloride injection, particularly in combination with a beta-blocker, in patients with CHF or significant left ventricular dysfunction.

Use in Patients with Pheochromocytoma

Only limited clinical experience exists in use of nicardipine hydrochloride injection for patients with hypertension associated with pheochromocytoma. Caution should therefore be exercised when using the drug in these patients.

Peripheral Vein Infusion Site

To minimize the risk of peripheral venous irritation, it is recommended that the site of infusion of nicardipine hydrochloride injection be changed every 12 hours.

PRECAUTIONS

General

Blood Pressure

Because nicardipine hydrochloride injection decreases peripheral resistance, monitoring of blood pressure during administration is required. Nicardipine hydrochloride injection, like other calcium channel blockers, may occasionally produce symptomatic hypotension. Caution is advised to avoid systemic hypotension when administering the drug to patients who have sustained an acute cerebral infarction or hemorrhage.

Use in Patients with Impaired Hepatic Function

Since nicardipine is metabolized in the liver, the drug should be used with caution in patients with impaired liver function or reduced hepatic blood flow. The use of lower dosages should be considered.

Nicardipine administered intravenously has been reported to increase hepatic venous pressure gradient by 4 mmHg in cirrhotic patients at high doses (5 mg/20 min). Nicardipine hydrochloride injection should therefore be used with caution in patients with portal hypertension.

Use in Patients with Impaired Renal Function

When nicardipine hydrochloride injection was given to mild to moderate hypertensive patients with moderate renal impairment, a significantly lower systemic clearance and higher AUC was observed. These results are consistent with those seen after oral administration of nicardipine. Careful dose titration is advised when treating renal impaired patients.

Drug Interactions

Since nicardipine hydrochloride injection may be administered to patients already being treated with other medications, including other antihypertensive agents, careful monitoring of these patients is necessary to detect and promptly treat any undesired effects from concomitant administration.

Beta-Blockers

In most patients, nicardipine hydrochloride injection can safely be used concomitantly with beta-blockers. However, caution should be exercised when using nicardipine hydrochloride injection in combination with a beta-blocker in congestive heart failure patients (see WARNINGS).

Cimetidine

Cimetidine has been shown to increase nicardipine plasma concentrations with nicardipine hydrochloride capsule administration. Patients receiving the two drugs concomitantly should be carefully monitored. Data with other histamine-2 antagonists are not available.

Digoxin

Studies have shown that nicardipine hydrochloride capsules usually do not alter digoxin plasma concentrations. However, as a precaution, digoxin levels should be evaluated when concomitant therapy with nicardipine hydrochloride injection is initiated.

Fentanyl Anesthesia

Hypotension has been reported during fentanyl anesthesia with concomitant use of a beta-blocker and a calcium channel blocker. Even though such interactions were not seen during clinical studies with nicardipine hydrochloride injection, an increased volume of circulating fluids might be required if such an interaction were to occur.

Cyclosporine

Concomitant administration of nicardipine hydrochloride capsules and cyclosporine results in elevated plasma cyclosporine levels. Plasma concentrations of cyclosporine should therefore be closely monitored during nicardipine hydrochloride injection administration, and the dose of cyclosporine reduced accordingly.

In Vitro Interaction

The plasma protein binding of nicardipine was not altered when therapeutic concentrations of furosemide, propranolol, dipyridamole, warfarin, quinidine, or naproxen were added to human plasma in vitro.

Carcinogenesis, Mutagenesis, Impairment of Fertility

Rats treated with nicardipine in the diet (at concentrations calculated to provide daily dosage levels of 5, 15, or 45 mg/kg/day) for two years showed a dose-dependent increase in thyroid hyperplasia and neoplasia (follicular adenoma/carcinoma). One- and three-month studies in the rat have suggested that these results are linked to a nicardipine-induced reduction in plasma thyroxine (T4) levels with a consequent increase in plasma levels of thyroid stimulating hormone (TSH). Chronic elevation of TSH is known to cause hyperstimulation of the thyroid. In rats on an iodine deficient diet, nicardipine administration for one month was associated with thyroid hyperplasia that was prevented by T4 supplementation. Mice treated with nicardipine in the diet (at concentrations calculated to provide daily dosage levels of up to 100 mg/kg/day) for up to 18 months showed no evidence of neoplasia of any tissue and no evidence of thyroid changes. There was no evidence of thyroid pathology in dogs treated with up to 25 mg nicardipine/kg/day for one year and no evidence of effects of nicardipine on thyroid function (plasma T4 and TSH) in man. There was no evidence of a mutagenic potential of nicardipine in a battery of genotoxicity tests conducted on microbial indicator organisms, in micronucleus tests in mice and hamsters, or in a sister chromatid exchange study in hamsters. No impairment of fertility was seen in male or female rats administered nicardipine at oral doses as high as 100 mg/kg/day (50 times the 40 mg TlD maximum recommended dose in man, assuming a patient weight of 60 kg).

Pregnancy

Pregnancy Category C

Nicardipine hydrochloride injection at doses up to 5 mg/kg/day to pregnant rats and up to 0.5 mg/kg/day to pregnant rabbits produced no embryotoxicity or teratogenicity. Embryotoxicity was seen at 10 mg/kg/day in rats and at 1 mg/kg/day in rabbits, but no teratogenicity was observed at these doses.

Nicardipine was embryocidal when administered orally to pregnant Japanese White rabbits, during organogenesis, at 150 mg/kg/day (a dose associated with marked body weight gain suppression in the treated doe), but not at 50 mg/kg/day (25 times the maximum recommended dose in man). No adverse effects on the fetus were observed when New Zealand albino rabbits were treated, during organogenesis, with up to 100 mg nicardipine/kg/day (a dose associated with significant mortality in the treated doe). In pregnant rats administered nicardipine orally at up to 100 mg/kg/day (50 times the maximum recommended human dose) there was no evidence of embryolethality or teratogenicity. However, dystocia, reduced birth weights, reduced neonatal survival, and reduced neonatal weight gain were noted. There are no adequate and well-controlled studies in pregnant women. Nicardipine hydrochloride should be used during pregnancy only if the potential benefit justifies the potential risk to the fetus.

Nursing Mothers

Studies in rats have shown significant concentrations of nicardipine in maternal milk. For this reason, it is recommended that women who wish to breastfeed should not be given this drug.

Pediatric Use

Safety and efficacy in patients under the age of 18 have not been established.

Geriatric Use

The steady-state pharmacokinetics of nicardipine are similar in elderly hypertensive patients (> 65 years) and young healthy adults.

Clinical studies of nicardipine did not include sufficient numbers of subjects aged 65 and over to determine whether they respond differently from younger subjects. Other reported clinical experience has not identified differences in responses between the elderly and younger patients. In general, dose selection for an elderly patient should be cautious, usually starting at the low end of the dosing range, reflecting the greater frequency of decreased hepatic, renal or cardiac function, and of concomitant disease or other drug therapy.

ADVERSE REACTIONS

Two hundred forty-four patients participated in two multicenter, double-blind, placebo-controlled trials of nicardipine hydrochloride injection. Adverse experiences were generally not serious and most were expected consequences of vasodilation. Adverse experiences occasionally required dosage adjustment. Therapy was discontinued in approximately 12% of patients, mainly due to hypotension, headache, and tachycardia.

Percent of Patients with Adverse Experiences During the Double-Blind Portion of Controlled Trials
Adverse Experience | Nicardipine Hydrochloride (n=144) | Placebo (n=100)
Body as a Whole
Headache | 14.6 | 2.0
Asthenia | 0.7 | 0.0
Abdominal pain | 0.7 | 0.0
Chest pain | 0.7 | 0.0
Cardiovascular
Hypotension | 5.6 | 1.0
Tachycardia | 3.5 | 0.0
ECG abnormality | 1.4 | 0.0
Postural hypotension | 1.4 | 0.0
Ventricular extrasystoles | 1.4 | 0.0
Extrasystoles | 0.7 | 0.0
Hemopericardium | 0.7 | 0.0
Hypertension | 0.7 | 0.0
Supraventricular tachycardia | 0.7 | 0.0
Syncope | 0.7 | 0.0
Vasodilation | 0.7 | 0.0
Ventricular tachycardia | 0.7 | 0.0
Digestive
Nausea/vomiting | 4.9 | 1.0
Injection Site
Injection site reaction | 1.4 | 0.0
Injection site pain | 0.7 | 0.0
Metabolic and Nutritional
Hypokalemia | 0.7 | 0.0
Nervous
Dizziness | 1.4 | 0.0
Hypesthesia | 0.7 | 0.0
Intracranial hemorrhage | 0.7 | 0.0
Paresthesia | 0.7 | 0.0
Respiratory
Dyspnea | 0.7 | 0.0
Skin and Appendages
Sweating | 1.4 | 0.0
Urogenital
Polyuria | 1.4 | 0.0
Hematuria | 0.7 | 0.0

Rare Events

The following rare events have been reported in clinical trials or in the literature in association with the use of intravenously administered nicardipine.

Body as a Whole

fever, neck pain

Cardiovascular

angina pectoris, atrioventricular block, ST segment depression, inverted T wave, deep-vein thrombophlebitis

Digestive

dyspepsia

Hemic and Lymphatic

thrombocytopenia

Metabolic and Nutritional

hypophosphatemia, peripheral edema

Nervous

confusion, hypertonia

Respiratory

respiratory disorder

Special Senses

conjunctivitis, ear disorder, tinnitus

Urogenital

urinary frequency

Sinus node dysfunction and myocardial infarction, which may be due to disease progression, have been seen in patients on chronic therapy with orally administered nicardipine.

OVERDOSAGE

Several overdosages with orally administered nicardipine have been reported. One adult patient allegedly ingested 600 mg of nicardipine [standard (immediate release) capsules], and another patient, 2160 mg of the sustained release formulation of nicardipine. Symptoms included marked hypotension, bradycardia, palpitations, flushing, drowsiness, confusion and slurred speech. All symptoms resolved without sequelae. An overdosage occurred in a one-year-old child who ingested half of the powder in a 30 mg nicardipine standard capsule. The child remained asymptomatic.

Based on results obtained in laboratory animals, lethal overdose may cause systemic hypotension, bradycardia (following initial tachycardia) and progressive atrioventricular conduction block. Reversible hepatic function abnormalities and sporadic focal hepatic necrosis were noted in some animal species receiving very large doses of nicardipine.

For treatment of overdosage, standard measures including monitoring of cardiac and respiratory functions should be implemented. The patient should be positioned so as to avoid cerebral anoxia. Frequent blood pressure determinations are essential. Vasopressors are clinically indicated for patients exhibiting profound hypotension. Intravenous calcium gluconate may help reverse the effects of calcium entry blockade.

DOSAGE AND ADMINISTRATION

Nicardipine hydrochloride injection is intended for intravenous use. DOSAGE MUST BE INDIVIDUALIZED depending upon the severity of hypertension and the response of the patient during dosing. Blood pressure should be monitored both during and after the infusion; too rapid or excessive reduction in either systolic or diastolic blood pressure during parenteral treatment should be avoided.

Preparation

Dilution:

Nicardipine hydrochloride injection is administered by slow continuous infusion at a CONCENTRATION OF 0.1 mg/mL. Each vial (25 mg) should be diluted with 240 mL of compatible intravenous fluid (see below), resulting in 250 mL of solution at a concentration of 0.1 mg/mL.

Nicardipine hydrochloride injection has been found to be compatible and stable in glass or polyvinyl chloride containers for 24 hours at controlled room temperature with:

Dextrose (5%) Injection, USP
Dextrose (5%) and Sodium Chloride (0.45%) Injection, USP
Dextrose (5%) and Sodium Chloride (0.9%) Injection, USP
Dextrose (5%) with 40 mEq Potassium, USP
Sodium Chloride (0.45%) Injection, USP
Sodium Chloride (0.9%) Injection, USP

Nicardipine hydrochloride injection is NOT compatible with Sodium Bicarbonate (5%) Injection, USP or Lactated Ringer’s Injection, USP.

THE DILUTED SOLUTION IS STABLE FOR 24 HOURS AT ROOM TEMPERATURE.

Inspection:

As with all parenteral drugs, nicardipine hydrochloride injection should be inspected visually for particulate matter and discoloration prior to administration, whenever solution and container permit. Nicardipine hydrochloride injection is normally light yellow in color.

Dosage

As a Substitute for Oral Nicardipine Therapy

The intravenous infusion rate required to produce an average plasma concentration equivalent to a given oral dose at steady state is shown in the following table:

Oral Nicardipine Hydrochloride Dose | Equivalent I.V. Infusion Rate
20 mg q8h | 0.5 mg/hr
30 mg q8h | 1.2 mg/hr
40 mg q8h | 2.2 mg/hr

For Initiation of Therapy in a Drug Free Patient

The time course of blood pressure decrease is dependent on the initial rate of infusion and the frequency of dosage adjustment. Nicardipine hydrochloride injection is administered by slow continuous infusion at a CONCENTRATION OF 0.1 mg/mL. With constant infusion, blood pressure begins to fall within minutes. It reaches about 50% of its ultimate decrease in about 45 minutes and does not reach final steady state for about 50 hours.

When treating acute hypertensive episodes in patients with chronic hypertension, discontinuation of infusion is followed by a 50% offset of action in 30 ± 7 minutes but plasma levels of drug and gradually decreasing antihypertensive effects exist for about 50 hours.

Titration: For gradual reduction in blood pressure, initiate therapy at 50 mL/hr (5 mg/hr). If desired blood pressure reduction is not achieved at this dose, the infusion rate may be increased by 25 mL/hr (2.5 mg/hr) every 15 minutes up to a maximum of 150 mL/hr (15 mg/hr), until desired blood pressure reduction is achieved.

For more rapid blood pressure reduction, initiate therapy at 50 mL/hr (5 mg/hr). If desired blood pressure reduction is not achieved at this dose, the infusion rate may be increased by 25 mL/hr (2.5 mg/hr) every 5 minutes up to a maximum of 150 mL/hr (15 mg/hr), until desired blood pressure reduction is achieved. Following achievement of the blood pressure goal, the infusion rate should be decreased to 30 mL/hr (3 mg/hr).

Maintenance: The rate of infusion should be adjusted as needed to maintain desired response.

Conditions Requiring Infusion Adjustment

Hypotension or Tachycardia: If there is concern of impending hypotension or tachycardia, the infusion should be discontinued. When blood pressure has stabilized, infusion of nicardipine hydrochloride injection may be restarted at low doses such as 30 to 50 mL/hr (3 to 5 mg/hr) and adjusted to maintain desired blood pressure.

Infusion Site Changes: Nicardipine hydrochloride injection should be continued as long as blood pressure control is needed. The infusion site should be changed every 12 hours if administered via peripheral vein.

Impaired Cardiac, Hepatic, or Renal Function: Caution is advised when titrating nicardipine hydrochloride injection in patients with congestive heart failure or impaired hepatic or renal function (see PRECAUTIONS).

Transfer to Oral Antihypertensive Agents

If treatment includes transfer to an oral antihypertensive agent other than nicardipine hydrochloride capsules, therapy should generally be initiated upon discontinuation of nicardipine hydrochloride injection.

If nicardipine hydrochloride capsules are to be used, the first dose of a TID regimen should be administered 1 hour prior to discontinuation of the infusion.

HOW SUPPLIED

Nicardipine hydrochloride injection 25 mg/10 mL (2.5 mg/mL) single dose vials are available in cartons of 10 as follows:

25 mg/10 mL (2.5 mg/mL) – NDC 40042-047-10

Store at 20ºC to 25ºC (68ºF to 77ºF) [see USP Controlled Room Temperature].

Freezing does not adversely affect the product, but exposure to elevated temperatures should be avoided.

Protect from light. Store vials in carton until used.

Manufactured for:
PharmaForce, Inc.
Columbus, OH 43229

Revised August 2009